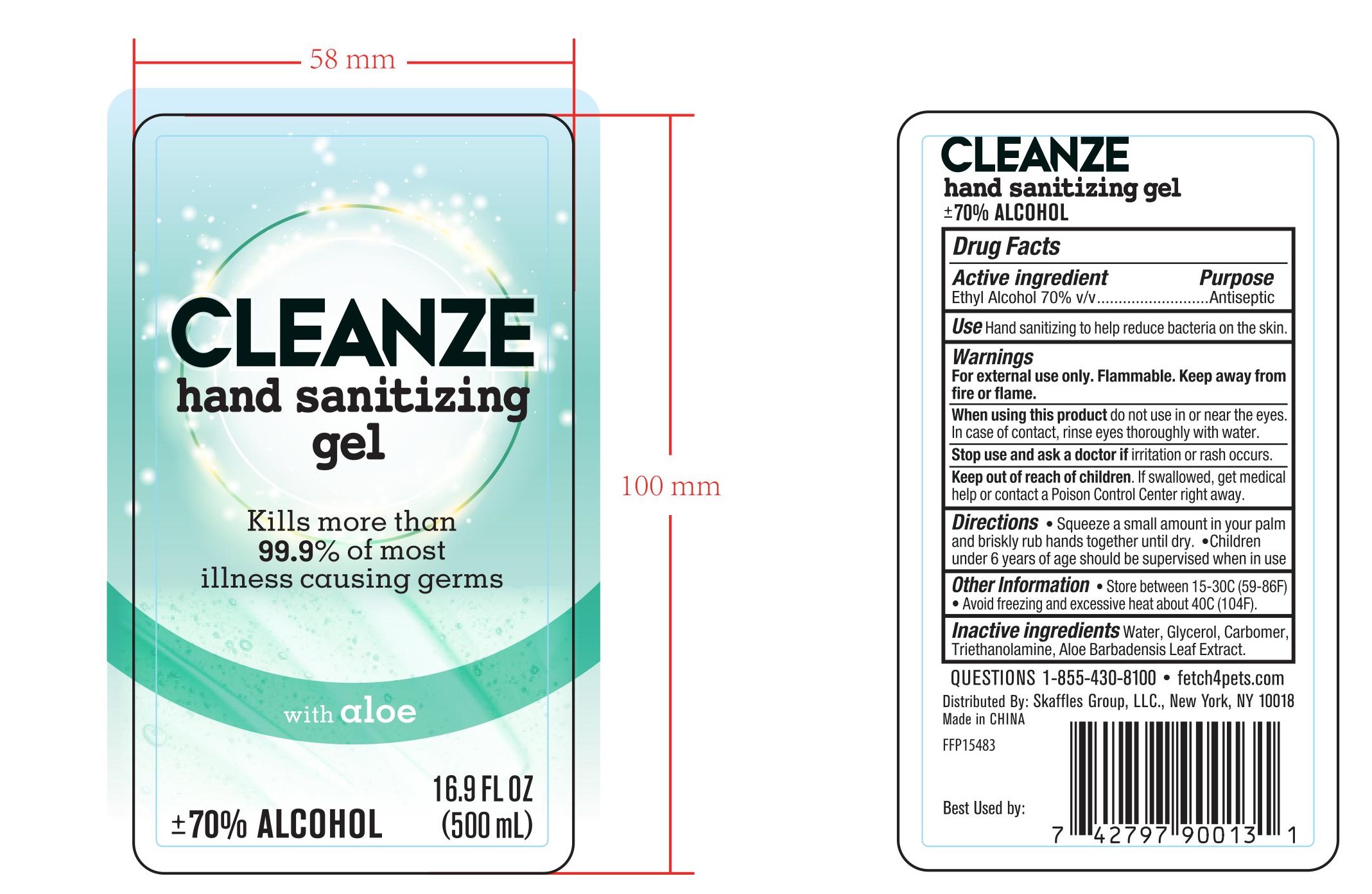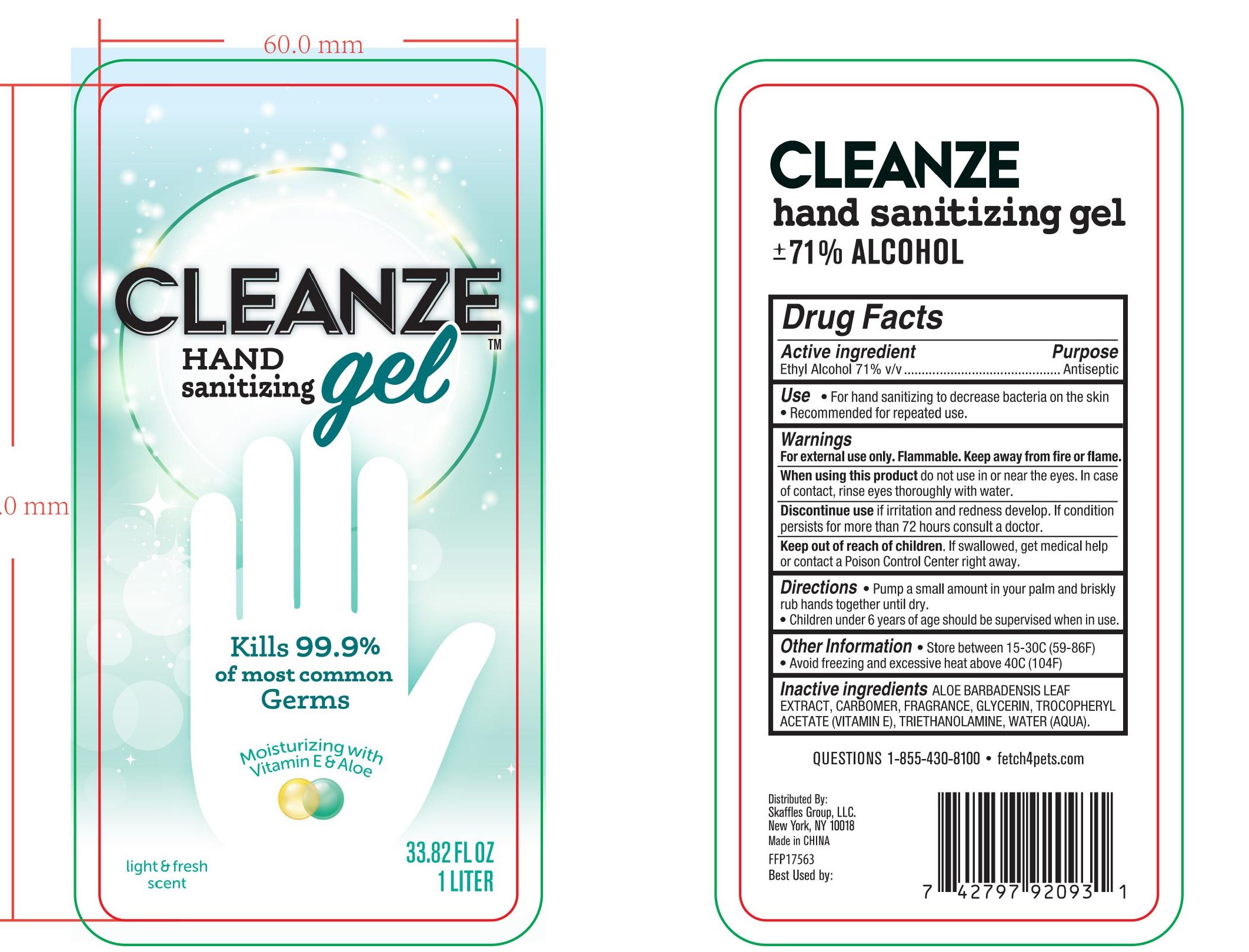 DRUG LABEL: CLEANZE HAND SANITIZING
NDC: 77720-016 | Form: GEL
Manufacturer: Skaffles Group Limited Liability Company
Category: otc | Type: HUMAN OTC DRUG LABEL
Date: 20210102

ACTIVE INGREDIENTS: ALCOHOL 71 mL/100 mL
INACTIVE INGREDIENTS: GLYCERIN; CARBOMER HOMOPOLYMER, UNSPECIFIED TYPE; ALOE VERA LEAF; WATER; TROLAMINE; ALPHA-TOCOPHEROL ACETATE

77720-016 CLEANZE SANITIZING GEL 70% Ethyl Alcohol

Active Ingredient

Ethyl Alcohol 71%

Purpose

Antiseptic

USE

For hand sanitizing to decrease bacteria on the skin
Recommended for repeated use.

Warning

For external use only. Flammable. Keep away from fire or flame. When using this product do not use in or near the eyes. In case of contact, rinse eyes thoroughly with water.
Discontinue use if irritation and redness develop. lf condition persists for more than 72 hours consult a physician.

Keep out of reach of children. If swallowed, get medical
help or contact a Poison Control Center right away.

Directions

Directions . Pump a small amount in your palm and briskly rub hands together until dry.
Children under 6 years of age should be supervised when in use. Other information . Store between 15 and 30C(59 and 86F).· Avoid freezing and excessive heat above 40C(104F).

Inactive ingredients

Aloe Barbadensis Leaf Extract, Carbomer,Glycerin,Tocopheryl Acetate (Vitamin E), Triethanolamine, Water(Aqua).